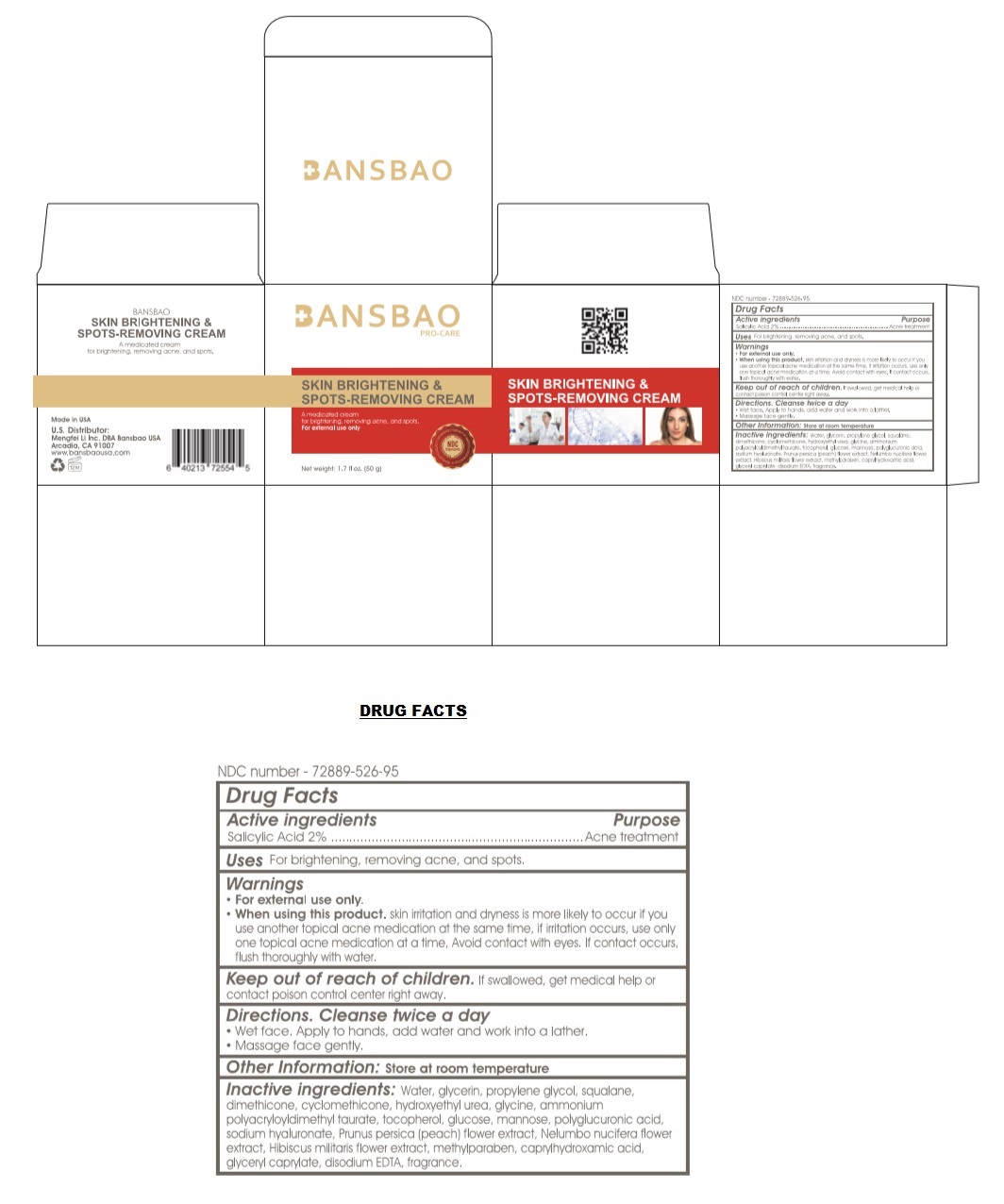 DRUG LABEL: BANSBAO SKIN BRIGHTENING AND SPOTS-REMOVING
NDC: 72889-526 | Form: CREAM
Manufacturer: Mengfei Li  Inc.
Category: otc | Type: HUMAN OTC DRUG LABEL
Date: 20190404

ACTIVE INGREDIENTS: SALICYLIC ACID 2 g/100 g
INACTIVE INGREDIENTS: WATER; GLYCERIN; PROPYLENE GLYCOL; SQUALANE; DIMETHICONE; CYCLOMETHICONE; HYDROXYETHYL UREA; GLYCINE ; AMMONIUM POLYACRYLOYLDIMETHYL TAURATE (55000 MPA.S) ; TOCOPHEROL ; ANHYDROUS DEXTROSE; MANNOSE, L-; POLYGALACTURONIC ACID ; HYALURONATE SODIUM; PRUNUS PERSICA FLOWER; NELUMBO NUCIFERA FLOWER ; HIBISCUS LAEVIS FLOWER; METHYLPARABEN; CAPRYLHYDROXAMIC ACID; GLYCERYL MONOCAPRYLATE; EDETATE DISODIUM ANHYDROUS; FAGRAEA BERTEROANA FLOWER OIL

BANSBAO SKIN BRIGHTENING & SPOTS-REMOVING CREAM

Active ingredients

Salicylic Acid 2%

Purpose

Acne treatment

Uses

For brightening, removing acne, and spots.

Warnings

- For external use only.
- When using this product. skin irritation and dryness is more likely to occur if you use another topical acne medication at the same time, if irritation occurs, use only one topical acne medication at a time, Avoid contact with eyes. If contact occurs, flush thoroughly with water.

Keep out of reach of children. If swallowed, get medical help or contact poison control center right away.

Direction. Cleanse twice a day

- Wet face. Apply to hands, add water and work into a lather.
- Massage face gently.

Other Information:

Store at room temperature

Inactive ingredients:

Water, glycerin, propylene glycol, squalane, dimethicone, cyclomethicone, hydroxyethyl urea, glycine, ammonium polyacryloyldimethyl taurate, tocopherol, glucose, mannose, polyglucuronic acid, sodium hyaluronate, Prunus persica (peach) flower extract, Nelumbo nucifera flower extract, Hibiscus militaris flower extract, methylparaben, caprylhydroxamic acid, glyceryl caprylate, disodium EDTA, fragrance.

Bansbao

PRO-CARE

A medicated cream for brightening, removing acne, and spots.

Made in USA

U.S. Distributor:

Mengfei Li Inc. DBA Bansbao USA

Arcadia, CA 91007

www.bansbaousa.com